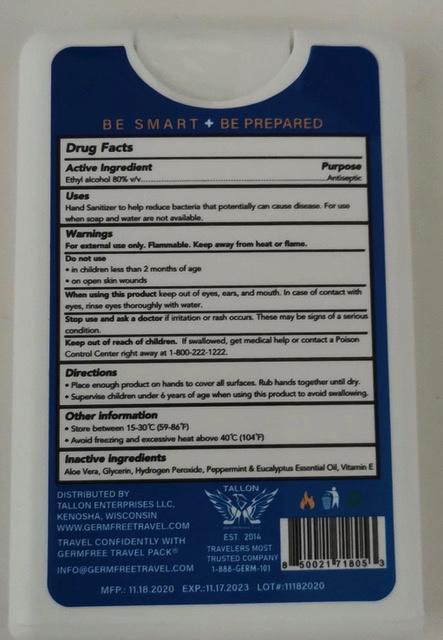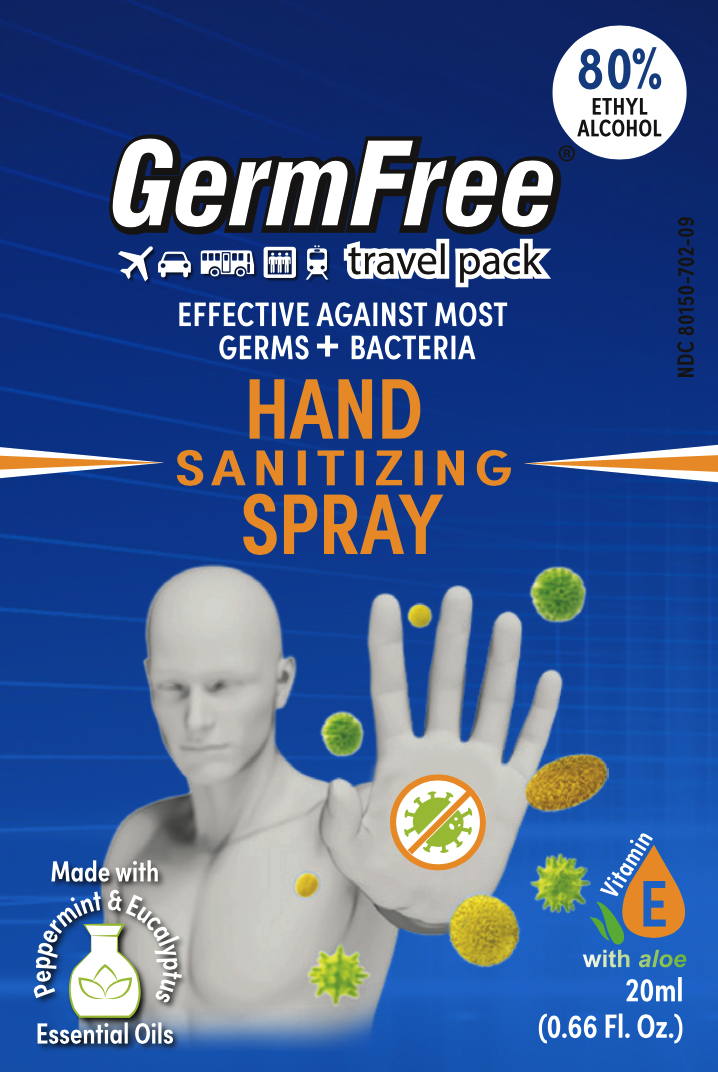 DRUG LABEL: GermFree Hand Sanitizing
NDC: 80150-702 | Form: SPRAY
Manufacturer: Tallon Enterprises LLC
Category: otc | Type: HUMAN OTC DRUG LABEL
Date: 20201123

ACTIVE INGREDIENTS: ALCOHOL 80 mL/100 mL
INACTIVE INGREDIENTS: PEPPERMINT OIL; ALOE VERA LEAF; EUCALYPTUS OIL; ALPHA-TOCOPHEROL; GLYCERIN 1.45 mL/100 mL; HYDROGEN PEROXIDE 0.125 mL/100 mL

GermFree Hand Sanitizing Spray

Active Ingredient(s)

Ethyl Alcohol 80% v/v.

Purpose

Antiseptic

Use

Hand Sanitizer to help reduce bacteria that potentially can cause disease. For use when soap and water are not available.

Warnings

For external use only. Flammable. Keep away from heat or flame

Do not use

- in children less than 2 months of age
- on open skin wounds

When using this product keep out of eyes, ears, and mouth. In case of contact with eyes, rinse eyes thoroughly with water.

Stop use and ask a doctor if irritation or rash occurs. These may be signs of a serious condition.

Keep out of reach of children. If swallowed, get medical help or contact a Poison Control Center right away at 1-800-222-1222.

Directions

- Place enough product on hands to cover all surfaces. Rub hands together until dry.
- Supervise children under 6 years of age when using this product to avoid swallowing.

Other information

- Store between 15-30C (59-86F)
- Avoid freezing and excessive heat above 40C (104F)

Inactive ingredients

aloe vera, glycerin, hydrogen peroxide, peppermint & eucalyptus essential oil, vitamin E

Package Label - Principal Display Panel

20mL NDC: 80150-702-09